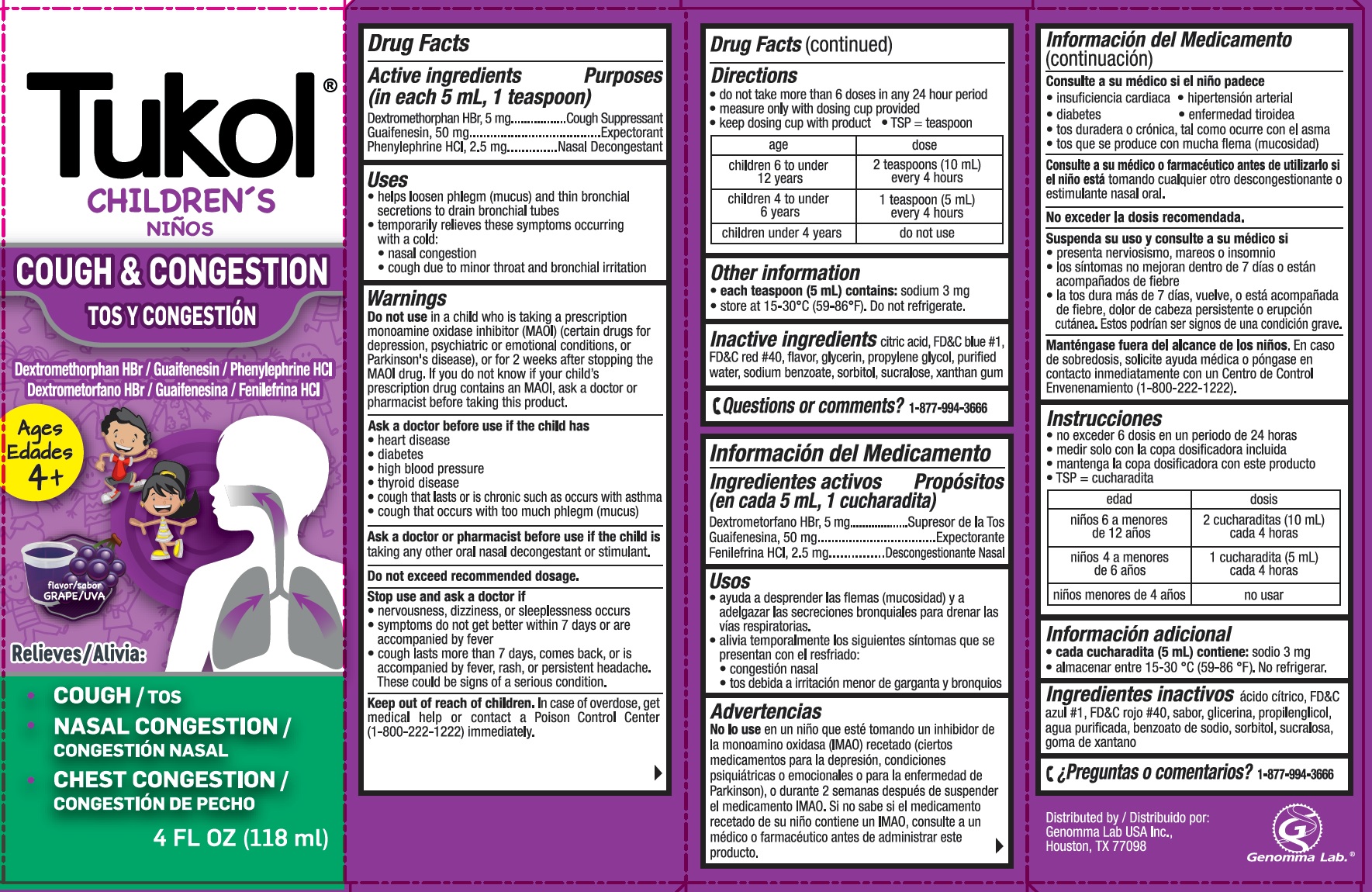 DRUG LABEL: Tukol Children Cough and Congestion
NDC: 50066-308 | Form: SYRUP
Manufacturer: Genomma Lab USA
Category: otc | Type: HUMAN OTC DRUG LABEL
Date: 20241011

ACTIVE INGREDIENTS: DEXTROMETHORPHAN HYDROBROMIDE 5 mg/5 mL; GUAIFENESIN 50 mg/5 mL; PHENYLEPHRINE HYDROCHLORIDE 2.5 mg/5 mL
INACTIVE INGREDIENTS: ANHYDROUS CITRIC ACID; FD&C BLUE NO. 1; FD&C RED NO. 40; GLYCERIN; PROPYLENE GLYCOL; WATER; SODIUM BENZOATE; SORBITOL; SUCRALOSE; XANTHAN GUM

Tukol® Children's Cough & Congestion Syrup

Drug Facts

ACTIVE INGREDIENT

Active Ingredient (in each 5 mL or 1 teaspoon) | Purpose
Dextromethorphan HBr, 5 mg | Cough Suppressant
Guaifenesin, 50 mg | Expectorant
Phenylephrine HCl, 2.5 mg | Nasal Decongestant

Uses

- helps loosen phlegm (mucus) and thin bronchial secretions to drain bronchial tubes
- temporarily relieves these symptoms occurring with a cold:
  - nasal congestion
  - cough due to minor throat and bronchial irritation

Warnings

Do not use in a child who is taking a prescription monoamine oxidase inhibitor (MAOI) (certain drugs for depression, psychiatric, or emotional conditions, or Parkinson's disease), or for 2 weeks after stopping the MAOI drug. If you do not know if your child's prescription drug contains an MAOI, ask a doctor or pharmacist before taking this product.

Ask a doctor before use if the child has

- heart disease
- high blood pressure
- thyroid disease
- diabetes
- cough that lasts or is chronic such as occurs with smoking, asthma, chronic bronchitis or emphysema
- cough that occurs with too much phlegm (mucus)

Ask a doctor or pharmacist before use if the child istaking any other oral nasal decongestant or stimulant.

Do not exceed recommended dosage.

Stop use and ask a doctor if

- nervousness, dizziness, or sleeplessness occurs
- symptoms do not get better within 7 days or are accompanied by fever
- cough lasts more than 7 days, comes back, or is accompanied by fever, rash, or persistant headache. These could be signs of a serious condition.

Keep out of reach of children. In case of overdose, get medical help or contact a Poison Control Center (1-800-222-1222) immediately.

Directions

- Do not take more than 6 doses in any 24 hour period
- measure only with dosing cup provided
- keep dosing cup with product
- TSP = teaspoon

age | dose
children 6 to under 12 years | 2 teaspoons (10 mL) every 4 hours
children 4 to under 6 years | 1 teaspoon (5 mL) every 4 hours
children under 4 years | do not use

Other information

- each teaspoon (5 mL) contains:sodium 3 mg
- store at 15-30°C (59-86°F). Do not refrigerate.

Inactive ingredients

citric acid, FD&C blue #1, FD&C red #40, flavor, glycerin, propylene glycol, purified water, sodium benzoate, sorbitol, sucralose, xanthan gum

Questions or comments?

1-877-994-3666

Distributed by:
Genomma Lab USA Inc.,
Houston, TX 77098

PRINCIPAL DISPLAY PANEL - 118 ml Bottle Carton

Tukol®

Children's

COUGH & CONGESTION

Dextromethorphan HBr / Guaifenesin / Phenylephrine HCl

Ages
4+

Relieves:

- COUGH
- NASAL CONGESTION
- CHEST CONGESTION

4 FL OZ (118 ml)